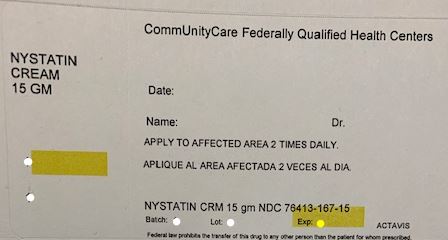 DRUG LABEL: Nystatin
NDC: 76413-167 | Form: CREAM
Manufacturer: Central Texas Community Health Centers
Category: prescription | Type: HUMAN PRESCRIPTION DRUG LABEL
Date: 20190204

ACTIVE INGREDIENTS: NYSTATIN 100000 [USP'U]/1 g
INACTIVE INGREDIENTS: ALUMINUM HYDROXIDE; CETOSTEARYL ALCOHOL; CITRIC ACID MONOHYDRATE; GLYCERYL MONOSTEARATE; POLYOXYL 40 STEARATE; PROPYLENE GLYCOL; PROPYLPARABEN; WATER; SODIUM CITRATE, UNSPECIFIED FORM; SORBIC ACID; SORBITOL; TITANIUM DIOXIDE; PETROLATUM; METHYLPARABEN

NYSTATIN CREAM USP

(100,000 units/g)

Rx Only

DESCRIPTION

EACH GRAM OF NYSTATIN CREAM USP CONTAINS: 100,000 units in an aqueous cream base of aluminum hydroxide gel, cetearyl alcohol (and) ceteareth-20, citric acid, glyceryl stearate, methylparaben, polyoxyl 40 stearate, propylene glycol, propylparaben, purified water, sodium citrate, sorbic acid, sorbitol solution, titanium dioxide and white petrolatum.

CLINICAL PHARMACOLOGY

Nystatin is an antifungal antibiotic which is both fungistatic and fungicidal in vitro against a wide variety of yeasts and yeast-like fungi. It probably acts by binding to sterols in the cell membrane of the fungus with a resultant change in membrane permeability allowing leakage of intracellular components. Nystatin is a polyene antibiotic of undetermined structural formula that is obtained from Streptomyces noursei, and is the first well tolerated antifungal antibiotic of dependable efficacy for the treatment of cutaneous, oral and intestinal infections caused by Candida (Monilia) albicans and other Candida species. It exhibits no appreciable activity against bacteria.

Nystatin provides specific therapy for all localized forms of candidiasis. Symptomatic relief is rapid, often occurring within 24 to 72 hours after the initiation of treatment. Cure is effected both clinically and mycologically in most cases of localized candidiasis.

INDICATIONS AND USAGE

Nystatin Cream USP is indicated in the treatment of cutaneous or mucocutaneous mycotic infections caused by Candida (Monilia) albicans and other Candida species.

CONTRAINDICATIONS

Nystatin Cream USP is contraindicated in patients with a history of hypersensitivity to any of its components.

PRECAUTIONS

Should a reaction of hypersensitivity occur the drug should be immediately withdrawn and appropriate measures taken.

This preparation is not for ophthalmic use.

ADVERSE REACTIONS

Nystatin is virtually nontoxic and nonsensitizing and is well tolerated by all age groups including debilitated infants, even on prolonged administration.

If irritation on topical application should occur, discontinue medication.

DOSAGE AND ADMINISTRATION

Nystatin Cream USP should be applied liberally to the affected areas twice a day or as indicated until healing is complete. Nystatin cream is usually preferred to nystatin ointment in candidiasis involving intertriginous areas; very moist lesions however are best treated with nystatin topical powder.

The cream does not stain the skin or mucous membranes and it provides a simple, convenient means of treatment.

HOW SUPPLIED

Product: 76413-167

NDC: 76413-167-15 1 g in a CARTON